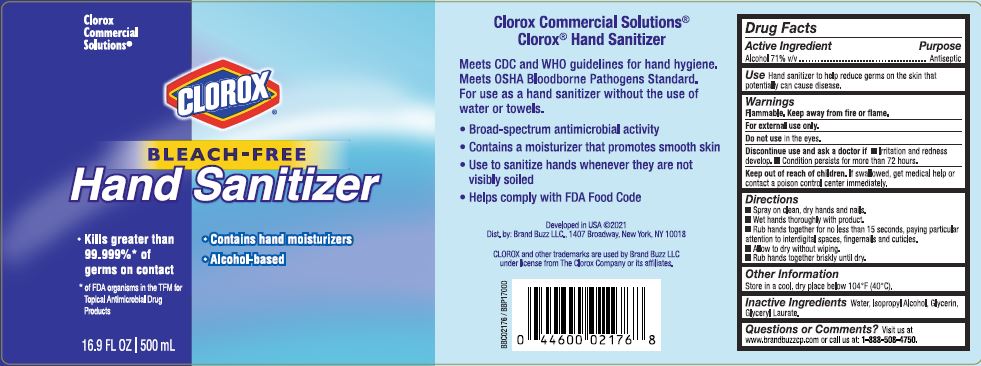 DRUG LABEL: Clorox Hand Sanitizer
NDC: 26509-0106 | Form: SOLUTION
Manufacturer: The Clorox Company
Category: otc | Type: HUMAN OTC DRUG LABEL
Date: 20210421

ACTIVE INGREDIENTS: ALCOHOL 71 mL/100 mL
INACTIVE INGREDIENTS: WATER; GLYCERYL LAURATE; GLYCERIN; ISOPROPYL ALCOHOL

Active Ingredient

Alcohol 71% v/v

Purpose

Antiseptic

Use

Hand sanitizer to help decrease bacteria on skin that can potentially cause disease.

Warnings

Flammable. Keep away from fire or flame.

For external use only.

Do not use in the eyes.

Discontinue use and ask a doctor if

- irritation and redness develop.
- condition persists for more than 72 hours.

Keep out of reach of children. If swallowed, get medical help or contact a poison control center immediately.

DIrections

- Spray on clean, dry hands and nails
- Wet hands thoroughly with product
- Rub hands together for no less than 15 seconds, paying particular attention to interdigital spaces, fingernails and cuticles
- Allow to dry without wiping
- Rub hands together briskly until dry

Other Information

- Store in a cool, dry place below 104 deg F (40 C)

Inactive Ingredients

Water, Isopropyl Alcohol, Glycerin, Glyceryl Laurate

Questions or Comments?

Visit us at www.brandbuzzcp.com or call us at: 1-888-508-4750.

PACKAGE LABEL

Clorox

Commercial

Solutions

CLOROX

BLEACH-FREE

Hand Sanitizer

Kills greater than

99.999%* of

germs on contact

Contains hand moisturizers

Alcohol-based

*of FDA organisms in the TFM for

Topical Antimicrobial Drug

Products

16.9 FL OZ I 500 mL